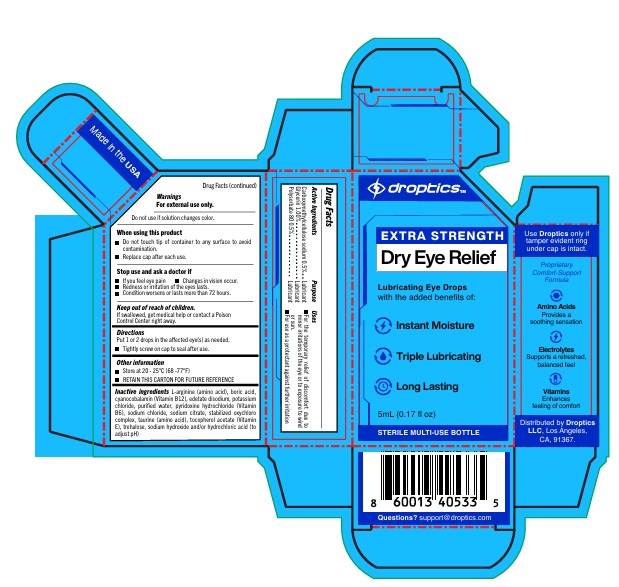 DRUG LABEL: Droptics Dry Eye Relief
NDC: 85211-002 | Form: LIQUID
Manufacturer: Droptics LLC
Category: otc | Type: HUMAN OTC DRUG LABEL
Date: 20260202

ACTIVE INGREDIENTS: CARBOXYMETHYLCELLULOSE SODIUM 0.5 g/100 mL; GLYCERIN 1 g/100 mL; POLYSORBATE 80 0.5 g/100 mL
INACTIVE INGREDIENTS: ARGININE; EDETATE DISODIUM; BORIC ACID; CYANOCOBALAMIN; POTASSIUM CHLORIDE; WATER; PYRIDOXINE HYDROCHLORIDE; SODIUM CHLORIDE; SODIUM CITRATE; SODIUM CHLORITE; TAURINE; .ALPHA.-TOCOPHEROL ACETATE; TREHALOSE; SODIUM HYDROXIDE; HYDROCHLORIC ACID

Active Ingredients

Carboxymethylcellulose sodium 0.5%
Glycerin 1%
Polysorbate 80 0.5%

Purpose

Lubricant

Uses

For the temporary relief of discomfort due to minor irritations of the eye or to exposure to wind or sun
For use as a protectant against further irritation

Warnings

For external use only
Do not use if solution changes color
When using this product
• Do not touch tip of the container to any surface to avoid contamination
• Replace cap after each use
Stop use and ask a doctor if
• If you feel eye pain
• Changes in vision occur
• Redness or irritation of the eye lasts
• Condition worsens or lasts more than 72 hours
Keep out of reach of children
• If swallowed, get medical help or contact a Poison Control Center right away

Directions

Put 1 or 2 drops in the affected eye(s) as needed.

- Tightly screw on cap to seal after use.

Other information

Store at 20 - 25°C (68 -77°F)

Inactive ingredients

L-arginine (amino acid), boric acid, cyanocobalamin (Vitamin B12), edetate disodium, potassium chloride, purified water, pyridoxine hydrochloride (Vitamin B6), sodium chloride, sodium citrate, stabilized oxychloro complex, taurine (amino acid), tocopherol acetate (Vitamin E), trehalose, sodium hydroxide and/or hydrochloric acid (to adjust pH)